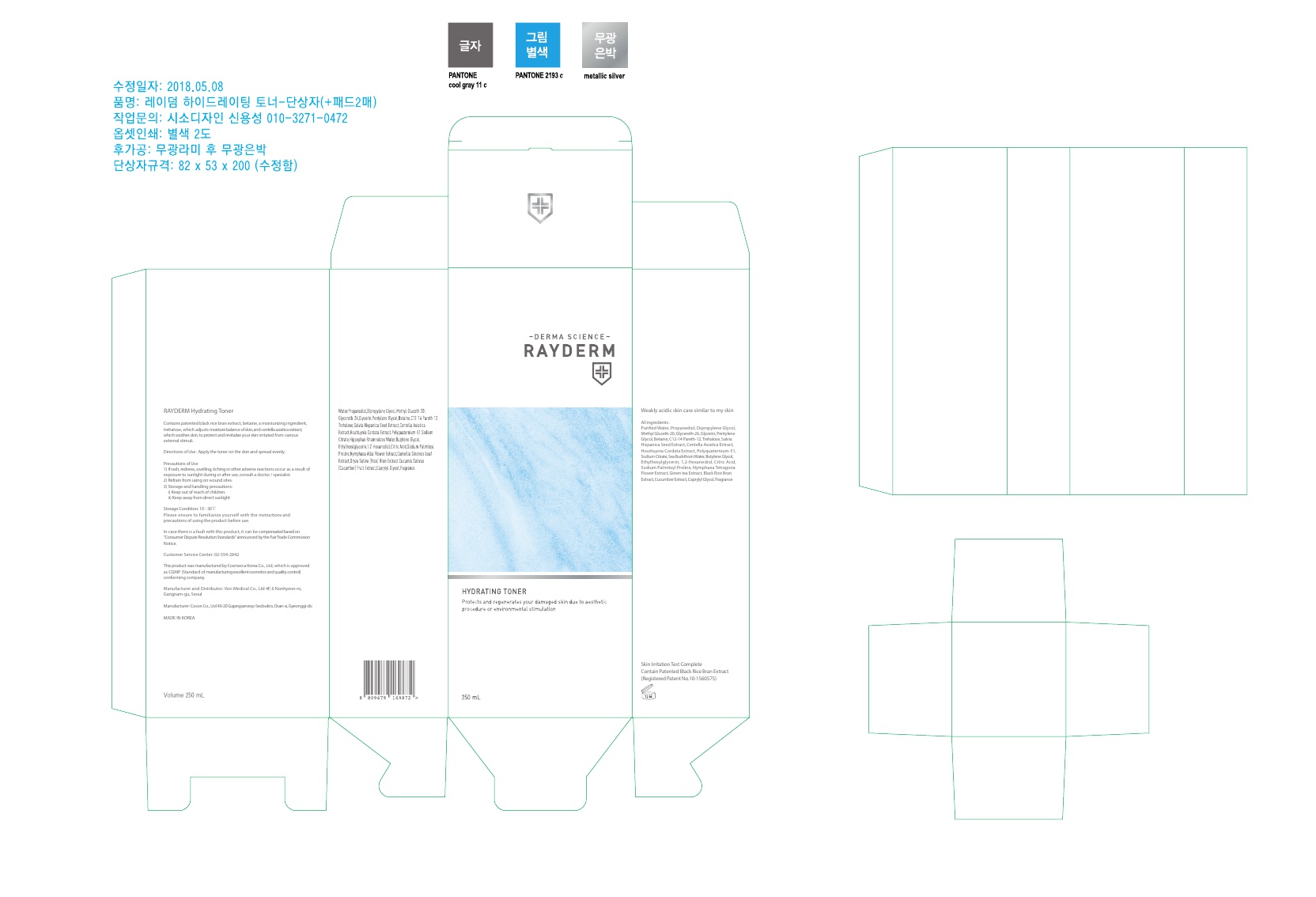 DRUG LABEL: Rayderm Hydrating Toner
NDC: 72543-004 | Form: LIQUID
Manufacturer: VORY MEDICAL. Inc
Category: otc | Type: HUMAN OTC DRUG LABEL
Date: 20181011

ACTIVE INGREDIENTS: glycerin 6.25 g/250 mL
INACTIVE INGREDIENTS: water; PROPANEDIOL; DIPROPYLENE GLYCOL; METHYL GLUCETH-20; GLYCERETH-26; PENTYLENE GLYCOL; BETAINE; C12-14 PARETH-12; TREHALOSE; SALVIA HISPANICA SEED; CENTELLA ASIATICA; POLYQUATERNIUM-51 (2-METHACRYLOYLOXYETHYL PHOSPHORYLCHOLINE/N-BUTYL METHACRYLATE; 3:7); SODIUM CITRATE; BUTYLENE GLYCOL; ETHYLHEXYLGLYCERIN; 1,2-HEXANEDIOL; SODIUM PALMITOYL PROLINE; NYMPHAEA ALBA FLOWER

ACTIVE INGREDIENT

Glycerin (2.5%) - Skin Protectact

INACTIVE INGREDIENT

Purified Water, Propanediol, Dipropylene, Methyl Gluceth-20, Glycereth-26, Glycerin, Pentylene Glycol, Betaine, C12-14 Pareth-12, Trehalose, Salvia Hispanica Seed Extract, Centella Asiatica Extract, Houttuynia Cordata Extract, Polyquaternium-51, Sodium Citrate, Sea Buckthorn Water, Butylene Glycol, Ethylhexylglycerin, 1,2-Hexanediol, Citric Acid, Sodium Palmitoyl Proline, Nymphaea Tetragona Flower Extract, Green tea Extract, Black Rice Bran Extract, Cucumber Extract, Caprylyl Glycol, Fragrance

PURPOSE

Skin Protectact

WARNINGS

Precautions of Use
1) If rash, redness, swelling, itching or other adverse reactions occur as a result of exposure to sunlight during or after use, consult a doctor / specialist.
2) Refrain from using on wound sites.
3) Storage and handling precautions:
i) Keep out of reach of children.
ii) Keep away from direct sunlight

INDICATIONS & USAGE

Apply the toner on the skin and spread evenly.

DOSAGE & ADMINISTRATION

Apply the toner on the skin and spread evenly.